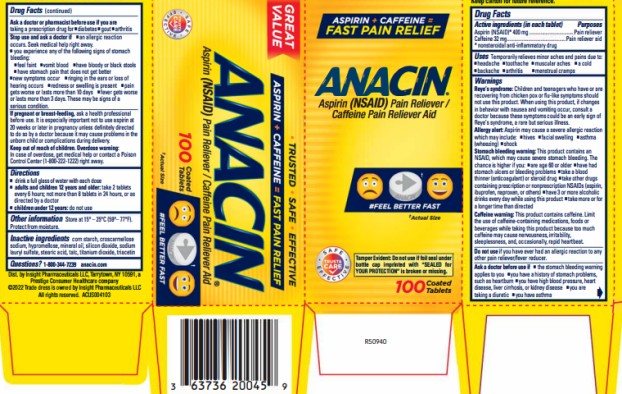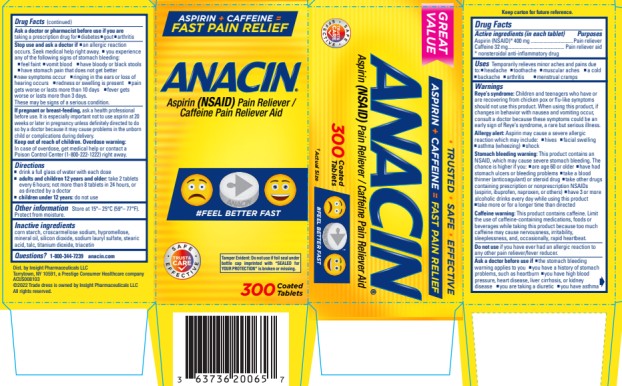 DRUG LABEL: Anacin
NDC: 63736-200 | Form: TABLET
Manufacturer: Insight Pharmaceuticals LLC
Category: otc | Type: HUMAN OTC DRUG LABEL
Date: 20251023

ACTIVE INGREDIENTS: ASPIRIN 400 mg/1 1; CAFFEINE 32 mg/1 1
INACTIVE INGREDIENTS: CROSCARMELLOSE SODIUM; HYPROMELLOSES; MINERAL OIL; SILICON DIOXIDE; SODIUM LAURYL SULFATE; STARCH, CORN; STEARIC ACID; TALC; TITANIUM DIOXIDE; TRIACETIN

Anacin - 63736-200

ANACIN- asprin and caffeine tablet Insight Pharmaceuticals

ANACIN®

Drug Facts

Active ingredients (per tablet)

Aspirin (NSAID)* 400 mg
Caffeine 32 mg

* nonsteroidal anti- inflammatory drug

Purposes

Pain reliever
Pain reliever aid

Uses

temporarily relieves minor aches and pains due to

- Headache
- toothache
- muscular aches
- a cold
- backache
- arthritis
- menstrual cramps

Warnings

Reye's syndrome: Children and teenagers who have or are recovering from chicken pox or flu-like symptoms should not use this product. When using this product, if changes in behavior with nausea and vomiting occur, consult a doctor because these symptoms could be an early sign of Reye's syndrome, a rare but serious illness.

Allergy alert:

Aspirin may cause a severe allergic reaction which may include:

- hives
- facial swelling
- asthma (wheezing)
- shock

Stomach bleeding warning

This product contains an NSAID, which may cause severe stomach bleeding. The chance is higher if you

- are age 60 or older
- have had stomach ulcers or bleeding problems
- take a blood thinner (anticoagulant) or steroid drug
- take other drugs containing prescription or nonprescription NSAIDs (aspirin, ibuprofen, naproxen, or others)
- have 3 or more alcoholic drinks every day while using this product
- take more or for a longer time than directed

Caffeine warning

This product contains caffeine. Limit the use of caffeine-containing medications, foods or beverages while taking this product because too much caffeine may cause nervousness, irritability, sleeplessness, and, occasionally, rapid heartbeat.

Do not use

if you have ever had an allergic reaction to any other pain reliever/fever reducer

Ask a doctor before use if

- the stomach bleeding warning applies to you
- you have a history of stomach problems, such as heartburn
- you have high blood pressure, heart disease, liver cirrhosis, or kidney disease
- you are taking a diuretic
- you have asthma

Ask a doctor or pharmacist before use if

you are taking a prescription drug for

- diabetes
- gout
- arthritis

Stop use and ask a doctor if

- an allergic reaction occurs. Seek medical help right away.
- you experience any of the following signs of stomach bleeding
  - feel faint
  - vomit blood
  - have bloody or black stools
  - have stomach pain that does not get better

- new symptoms occur
- ringing in the ears or loss of hearing occurs
- redness or swelling is present
- pain gets worse or lasts more than 10 days
- fever gets worse or lasts more than 3 days
- These may be signs of a serious condition

If pregnant or breast-feeding,

ask a health professional before use. It is especially important not to use aspirin at least 20 weeks or later in pregnancy unless definitely directed to do so by a doctor because it may cause problems in the unborn child or complications during delivery.

Overdose warning

In case of overdose, get medical help or contact a Poison Control Center (1-800-222-1222) right away.

Directions

- drink a full glass of water with each dose
- adults and children 12 years of age and older: take 2 tablets every 6 hours; not more than 8 tablets in 24 hours, or as directed by a doctor
- children under 12 years of age: do not use

Other information

Keep carton for full drug facts and warnings.

Store at 15 – 25°C (59– 77°F). Protect from moisture.

Inactive ingredients

corn starch, croscarmellose sodium, hypromellose, mineral oil, , silicon dioxide, sodium lauryl sulfate, stearic acid, talc, titanium dioxide, triacetin

Questions?

1-800-344-7239 anacin.com

PRINCIPAL DISPLAY PANEL

ANACIN®

Aspirin (NSAID) Pain Reliever / Caffeine Pain Reliever Aid

100 COATED TABLETS

PRINCIPAL DISPLAY PANEL

ANACIN®

Aspirin (NSAID) Pain Reliever / Caffeine Pain Reliever Aid

300 COATED TABLETS